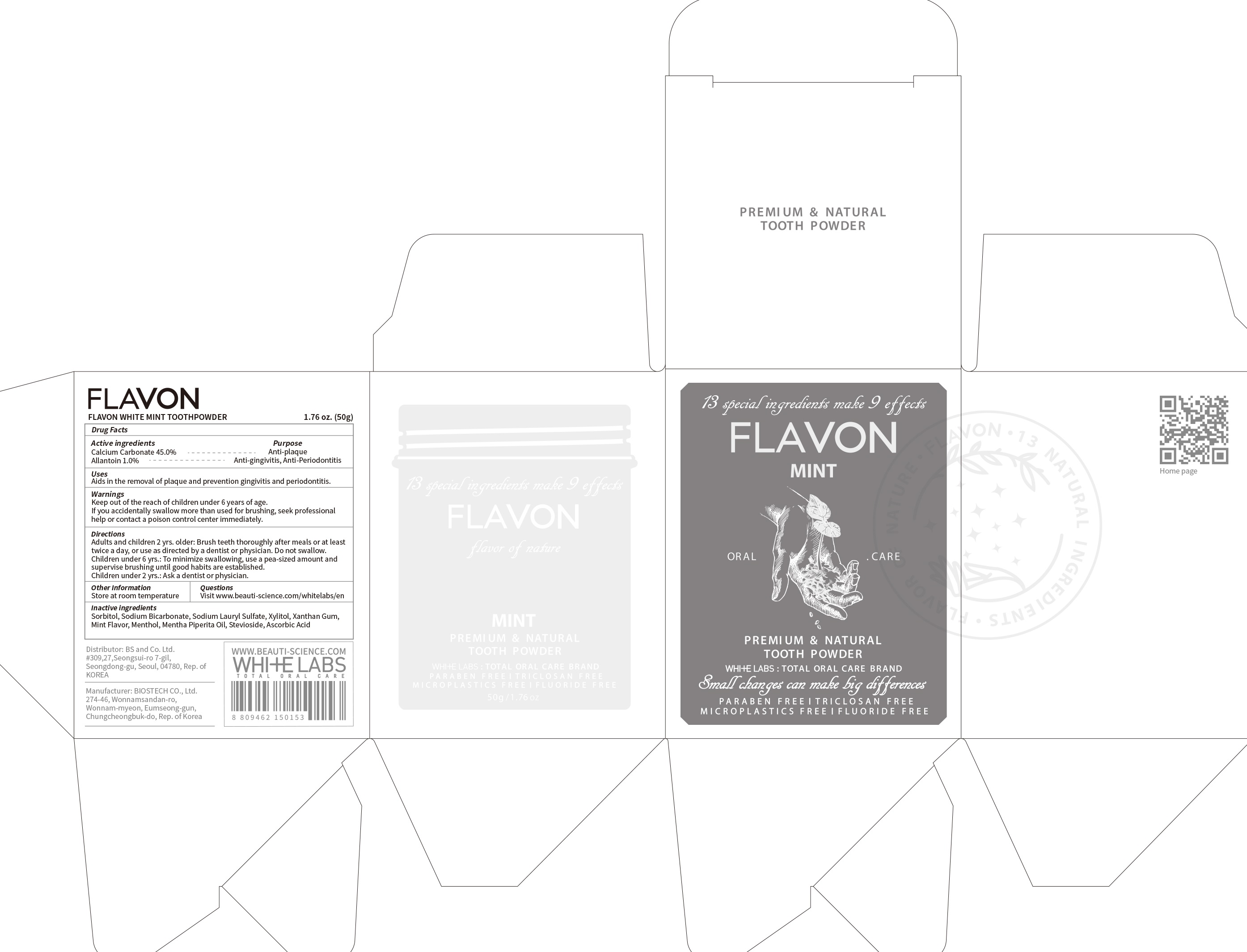 DRUG LABEL: FLAVON WHITE MINT TOOTH
NDC: 73660-003 | Form: POWDER, DENTIFRICE
Manufacturer: BS and Co. Ltd
Category: otc | Type: HUMAN OTC DRUG LABEL
Date: 20200725

ACTIVE INGREDIENTS: Calcium Carbonate 45.0 g/100 g; Allantoin 1.0 g/100 g
INACTIVE INGREDIENTS: Sorbitol; Sodium Bicarbonate; Sodium Lauryl Sulfate; Xylitol; Xanthan Gum; Menthol; PEPPERMINT OIL; Stevioside; ASCORBIC ACID

ACTIVE INGREDIENT

Calcium Carbonate 45.0%
Allantoin 1.0%

PURPOSE

Anti-plaque
Anti-gingivitis, Anti-Periodontitis

Uses

Aids in the removal of plaque and prevention gingivitis and periodontitis.

WARNINGS

Keep out of the reach of children under 6 years of age.
If you accidentally swallow more than used for brushing, seek professional help or contact a poison control center immediately.

KEEP OUT OF REACH OF CHILDREN

Keep out of the reach of children under 6 years of age.

Directions

Adults and children 2 yrs. older: Brush teeth thoroughly after meals or at least twice a day, or use as directed by a dentist or physician. Do not swallow.
Children under 6 yrs.: To minimize swallowing, use a pea-sized amount and supervise brushing until good habits are established.
Children under 2 yrs.: Ask a dentist or physician.

Other Information

Store at room temperature

QUESTIONS

Visit www.beauti-science.com/whitelabs/en

INACTIVE INGREDIENTS

Sorbitol, Sodium Bicarbonate, Sodium Lauryl Sulfate, Xylitol, Xanthan Gum, Mint Flavor, Menthol, Mentha Piperita Oil, Stevioside, Ascorbic Acid